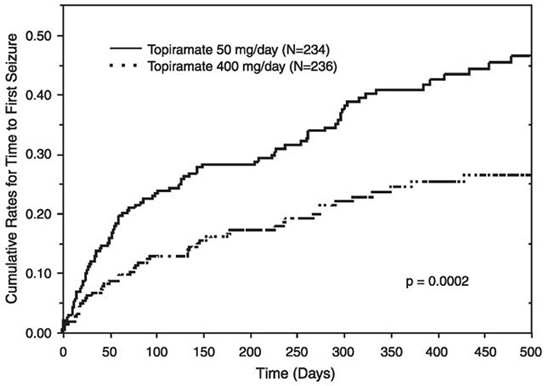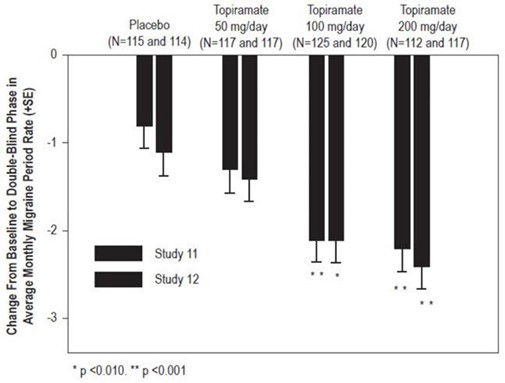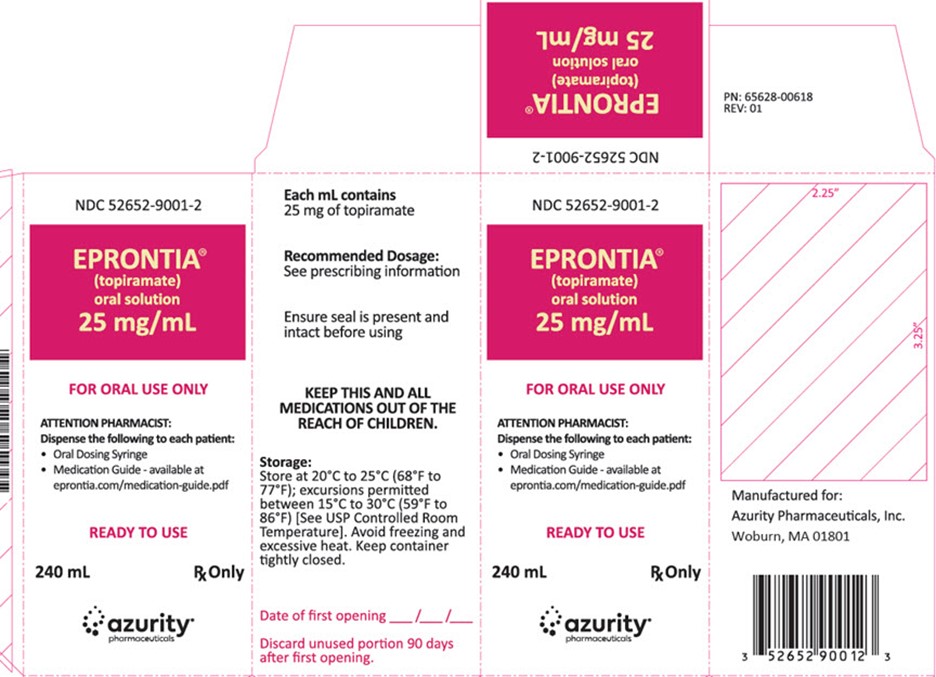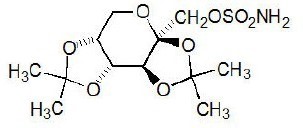 DRUG LABEL: Eprontia
NDC: 59368-405 | Form: SOLUTION
Manufacturer: Praxis, LLC
Category: prescription | Type: HUMAN PRESCRIPTION DRUG LABEL
Date: 20230101

ACTIVE INGREDIENTS: TOPIRAMATE 25 mg/1 mL
INACTIVE INGREDIENTS: POLYETHYLENE GLYCOL, UNSPECIFIED; METHYLPARABEN; PROPYLPARABEN; SUCRALOSE; GLYCERIN

EPRONTIA®(topiramate) oral solution

8 USE IN SPECIFIC POPULATIONS

8.1 Pregnancy

Pregnancy Exposure Registry

There is a pregnancy exposure registry that monitors pregnancy outcomes in women exposed to topiramate during pregnancy. Patients should be encouraged to enroll in the North American Antiepileptic Drug (NAAED) Pregnancy Registry if they become pregnant. This registry is collecting information about the safety of antiepileptic drugs during pregnancy. To enroll, patients can call the toll-free number 1-888-233-2334. Information about the North American Drug Pregnancy Registry can be found at http://www.aedpregnancyregistry.org/.

Risk Summary

Topiramate can cause fetal harm when administered to a pregnant woman. Data from pregnancy registries indicate that infants exposed to topiramate in uterohave an increased risk of major congenital malformations, including but not limited to cleft lip and/or cleft palate (oral clefts), and of being small for gestational age (SGA) [see Human Data] . SGA has been observed at all doses and appears to be dose-dependent. The prevalence of SGA is greater in infants of women who received higher doses of topiramate during pregnancy. In addition, the prevalence of SGA in infants of women who continued topiramate use until later in pregnancy is higher compared to the prevalence in infants of women who stopped topiramate use before the third trimester.

In multiple animal species, topiramate produced developmental toxicity, including increased incidences of fetal malformations, in the absence of maternal toxicity at clinically relevant doses [see Animal Data] .

All pregnancies have a background risk of birth defects, loss, or other adverse outcomes. The estimated background risk of major birth defects and miscarriage for the indicated population is unknown. In the U.S. general population, the estimated background risks of major birth defects and miscarriage in clinically recognized pregnancies are 2-4% and 15-20%, respectively.

Clinical Considerations

Fetal/Neonatal Adverse Reactions

Consider the benefits and risks of topiramate when prescribing this drug to women of childbearing potential, particularly when topiramate is considered for a condition not usually associated with permanent injury or death. Because of the risk of oral clefts to the fetus, which occur in the first trimester of pregnancy, all women of childbearing potential should be informed of the potential risk to the fetus from exposure to topiramate. Women who are planning a pregnancy should be counseled regarding the relative risks and benefits of topiramate use during pregnancy, and alternative therapeutic options should be considered for these patients.

Labor or Delivery

Although the effect of topiramate on labor and delivery in humans has not been established, the development of topiramate-induced metabolic acidosis in the mother and/or in the fetus might affect the fetus' ability to tolerate labor.

Topiramate treatment can cause metabolic acidosis [see Warnings and Precautions (5.4)] . The effect of topiramate-induced metabolic acidosis has not been studied in pregnancy; however, metabolic acidosis in pregnancy (due to other causes) can cause decreased fetal growth, decreased fetal oxygenation, and fetal death, and may affect the fetus' ability to tolerate labor. Pregnant patients should be monitored for metabolic acidosis and treated as in the nonpregnant state [see Warnings and Precautions (5.4)] . Newborns of mothers treated with topiramate should be monitored for metabolic acidosis because of transfer of topiramate to the fetus and possible occurrence of transient metabolic acidosis following birth.

Based on limited information, topiramate has also been associated with pre-term labor and premature delivery.

Data

Human Data

Data from pregnancy registries indicate an increased risk of major congenital malformations, including but not limited to oral clefts in infants exposed to topiramate during the first trimester of pregnancy. Other than oral clefts, no specific pattern of major congenital malformations or grouping of major congenital malformation types were observed. In the NAAED pregnancy registry, when topiramate-exposed infants with only oral clefts were excluded, the prevalence of major congenital malformations (4.1%) was higher than that in infants exposed to a reference AED (1.8%) or in infants with mothers without epilepsy and without exposure to AEDs (1.1%). The prevalence of oral clefts among topiramate-exposed infants (1.4%) was higher than the prevalence in infants exposed to a reference AED (0.3%) or the prevalence in infants with mothers without epilepsy and without exposure to AEDs (0.11%). It was also higher than the background prevalence in United States (0.17%) as estimated by the Centers for Disease Control and Prevention (CDC). The relative risk of oral clefts in topiramate-exposed pregnancies in the NAAED Pregnancy Registry was 12.5 (95% Confidence Interval [CI] 5.9 – 26.37) as compared to the risk in a background population of untreated women. The UK Epilepsy and Pregnancy Register reported a prevalence of oral clefts among infants exposed to topiramate monotherapy (3.2%) that was 16 times higher than the background rate in the UK (0.2%).

Data from the NAAED pregnancy registry and a population-based birth registry cohort indicate that exposure to topiramate in uterois associated with an increased risk of SGA newborns (birth weight <10th percentile). In the NAAED pregnancy registry, 19.7% of topiramate-exposed newborns were SGA compared to 7.9% of newborns exposed to a reference AED and 5.4% of newborns of mothers without epilepsy and without AED exposure. In the Medical Birth Registry of Norway (MBRN), a population-based pregnancy registry, 25% of newborns in the topiramate monotherapy exposure group were SGA compared to 9 % in the comparison group unexposed to AEDs. The long-term consequences of the SGA findings are not known.

Animal Data

When topiramate (0, 20, 100, or 500 mg/kg/day) was administered to pregnant mice during the period of organogenesis, incidences of fetal malformations (primarily craniofacial defects) were increased at all doses. Fetal body weights and skeletal ossification were reduced at the highest dose tested in conjunction with decreased maternal body weight gain. A no-effect dose for embryofetal developmental toxicity in mice was not identified. The lowest dose tested, which was associated with increased malformations, is less than the maximum recommended human dose (MRHD) for epilepsy (400 mg/day) or migraine (100 mg/day) on a body surface area (mg/m^2) basis.

In pregnant rats administered topiramate (0, 20, 100, and 500 mg/kg/day or 0, 0.2, 2.5, 30, and 400 mg/kg/day) orally during the period of organogenesis, the frequency of limb malformations (ectrodactyly, micromelia, and amelia) was increased in fetuses at 400 and 500 mg/kg/day. Embryotoxicity (reduced fetal body weights, increased incidences of structural variations) was observed at doses as low as 20 mg/kg/day. Clinical signs of maternal toxicity were seen at 400 mg/kg/day and above, and maternal body weight gain was reduced at doses of 100 mg/kg/day or greater. The no-effect dose (2.5 mg/kg/day) for embryofetal developmental toxicity in rats is less than the MRHD for epilepsy or migraine on a mg/m^2basis.

In pregnant rabbits administered topiramate (0, 20, 60, and 180 mg/kg/day or 0, 10, 35, and 120 mg/kg/day) orally during organogenesis, embryofetal mortality was increased at 35 mg/kg/day, and increased incidences of fetal malformations (primarily rib and vertebral malformations) were observed at 120 mg/kg/day. Evidence of maternal toxicity (decreased body weight gain, clinical signs, and/or mortality) was seen at 35 mg/kg/day and above. The no-effect dose (20 mg/kg/day) for embryofetal developmental toxicity in rabbits is equivalent to the MRHD for epilepsy and approximately 4 times the MRHD for migraine on a mg/m^2basis.

When topiramate (0, 0.2, 4, 20, and 100 mg/kg/day or 0, 2, 20, and 200 mg/kg/day) was administered orally to female rats during the latter part of gestation and throughout lactation, offspring exhibited decreased viability and delayed physical development at 200 mg/kg/day and reductions in pre- and/or postweaning body weight gain at 2 mg/kg/day and above. Maternal toxicity (decreased body weight gain, clinical signs) was evident at 100 mg/kg/day or greater. In a rat embryofetal development study which included postnatal assessment of offspring, oral administration of topiramate (0, 0.2, 2.5, 30, and 400 mg/kg) to pregnant animals during the period of organogenesis resulted in delayed physical development in offspring at 400 mg/kg/day and persistent reductions in body weight gain in offspring at 30 mg/kg/day and higher. The no-effect dose (0.2 mg/kg/day) for pre- and postnatal developmental toxicity in rats is less than the MRHD for epilepsy or migraine on a mg/m^2basis.

8.2 Lactation

Risk Summary

Topiramate is excreted in human milk [ see Data] . The effects of topiramate on milk production are unknown. Diarrhea and somnolence have been reported in breastfed infants whose mothers receive topiramate treatment. The developmental and health benefits of breastfeeding should be considered along with the mother's clinical need for topiramate and any potential adverse effects on the breastfed infant from topiramate or from the underlying maternal condition.

Data

Human Data

Limited data from 5 women with epilepsy treated with topiramate during lactation showed drug levels in milk similar to those in maternal plasma.

8.3 Females and Males of Reproductive Potential

Contraception

Women of childbearing potential who are not planning a pregnancy should use effective contraception because of the risk of major congenital malformations, including oral clefts, and the risk of infants being SGA [see Drug Interactions (7.4) and Use in Specific Populations (8.1)] .

8.4 Pediatric Use

Adjunctive Treatment for Epilepsy

Pediatric Patients 2 Years of Age and Older

The safety and effectiveness of EPRONTIA as adjunctive therapy for the treatment of partial-onset seizures, primary generalized tonic-clonic seizures, or seizures associated with Lennox-Gastaut syndrome have been established in pediatric patients 2 years of age and older [see Adverse Reactions (6.1) and Clinical Studies (14.2)] .

Pediatric Patients Below the Age of 2 Years

Safety and effectiveness in patients below the age of 2 years have not been established for the adjunctive therapy treatment of partial-onset seizures, primary generalized tonic-clonic seizures, or seizures associated with Lennox-Gastaut syndrome. In a single randomized, double-blind, placebo-controlled investigational trial, the efficacy, safety, and tolerability of topiramate oral liquid and sprinkle formulations as an adjunct to concurrent antiepileptic drug therapy in pediatric patients 1 to 24 months of age with refractory partial-onset seizures were assessed. After 20 days of double-blind treatment, topiramate (at fixed doses of 5, 15, and 25 mg/kg/day) did not demonstrate efficacy compared with placebo in controlling seizures.

In general, the adverse reaction profile for topiramate in this population was similar to that of older pediatric patients, although results from the above controlled study and an open-label, long-term extension study in these pediatric patients 1 to 24 months old suggested some adverse reactions/toxicities (not previously observed in older pediatric patients and adults; i.e., growth/length retardation, certain clinical laboratory abnormalities, and other adverse reactions/toxicities that occurred with a greater frequency and/or greater severity than had been recognized previously from studies in older pediatric patients or adults for various indications).

These very young pediatric patients appeared to experience an increased risk for infections (any topiramate dose 12%, placebo 0%) and of respiratory disorders (any topiramate dose 40%, placebo 16%). The following adverse reactions were observed in at least 3% of patients on topiramate and were 3% to 7% more frequent than in patients on placebo: viral infection, bronchitis, pharyngitis, rhinitis, otitis media, upper respiratory infection, cough, and bronchospasm. A generally similar profile was observed in older pediatric patients [see Adverse Reactions (6)] .

Topiramate resulted in an increased incidence of patients with increased creatinine (any topiramate dose 5%, placebo 0%), BUN (any topiramate dose 3%, placebo 0%), and protein (any topiramate dose 34%, placebo 6%), and an increased incidence of decreased potassium (any topiramate dose 7%, placebo 0%). This increased frequency of abnormal values was not dose-related. Creatinine was the only analyte showing a noteworthy increased incidence (topiramate 25 mg/kg/day 5%, placebo 0%) of a markedly abnormal increase. The significance of these findings is uncertain.

Topiramate treatment also produced a dose-related increase in the percentage of patients who had a shift from normal at baseline to high/increased (above the normal reference range) in total eosinophil count at the end of treatment. The incidence of these abnormal shifts was 6 % for placebo, 10% for 5 mg/kg/day, 9% for 15 mg/kg/day, 14% for 25 mg/kg/day, and 11% for any topiramate dose. There was a mean dose-related increase in alkaline phosphatase. The significance of these findings is uncertain.

Topiramate produced a dose-related increased incidence of hyperammonemia [see Warnings and Precautions (5.12)].

Treatment with topiramate for up to 1 year was associated with reductions in Z SCORES for length, weight, and head circumference [see Warnings and Precautions (5.4), Adverse Reactions (6)] .

In open-label, uncontrolled experience, increasing impairment of adaptive behavior was documented in behavioral testing over time in this population. There was a suggestion that this effect was dose-related. However, because of the absence of an appropriate control group, it is not known if this decrement in function was treatment-related or reflects the patient's underlying disease (e.g., patients who received higher doses may have more severe underlying disease) [see Warnings and Precautions (5.6)] .

In this open-label, uncontrolled study, the mortality was 37 deaths/1000 patient years. It is not possible to know whether this mortality rate is related to topiramate treatment, because the background mortality rate for a similar, significantly refractory, young pediatric population (1-24 months) with partial epilepsy is not known.

Monotherapy Treatment for Epilepsy

Pediatric Patients 2 Years of Age and Older

The safety and effectiveness of EPRONTIA as monotherapy for the treatment of partial-onset seizures or primary generalized tonic-clonic seizures have been established in pediatric patients aged 2 years and older [see Clinical Trials Experience (6.1), Clinical Studies (14.1)] .

A one-year, active-controlled, open-label study with blinded assessments of bone mineral density (BMD) and growth in pediatric patients 4 to 15 years of age, including 63 patients with recent or new onset of epilepsy, was conducted to assess effects of topiramate (N=28, 6-15 years of age) versus levetiracetam (N=35, 4-15 years of age) monotherapy on bone mineralization and on height and weight, which reflect growth. Effects on bone mineralization were evaluated via dual-energy X-ray absorptiometry and blood markers. Table 10summarizes effects of topiramate at 12 months for key safety outcomes including BMD, height, height velocity, and weight. All Least Square Mean values for topiramate and the comparator were positive. Therefore, the Least Square Mean treatment differences shown reflect a topiramate-induced attenuation of the key safety outcomes. Statistically significant effects were observed for decreases in BMD (and bone mineral content) in lumbar spine and total body less head and in weight. Subgroup analyses according to age demonstrated similar negative effects for all key safety outcomes (i.e., BMD, height, weight).

Table 10: Summary of Topiramate Treatment Difference Results at 12 Months for Key Safety Outcomes
Safety Parameter | Treatment Difference in Least Square Means (95 % Confidence Interval)
Annual Change in BMD Lumbar Spine (g/cm^2) | -0.036 (-0.058, -0.014)
Annual Change in BMD TBLH [TBLH=total body less head] (g/cm^2) | -0.026 (-0.039, -0.012)
Annual Change in Height (cm) (4-9 years, Primary Analysis Population for Height) [Whereas no patients were randomized to 2-5 year age subgroup for topiramate, 5 patients (4-5 years) were randomized to the active control group.] | -0.84 (-2.67, 0.99)
Annual Change in Height (cm) (4-15 years) | -0.75 (-2.21, 0.71)
Annual Change in Height (cm) (10-15 years) | -1.01 (-3.64, 1.61)
Height Velocity (cm/year) (4-9 years) | -1.00 (-2.76, 0.76)
Height Velocity (cm/year) (4-15 years) | -0.98 (-2.33, 0.37)
Height Velocity (cm/year) (10-15 years) | -0.96 (-3.24, 1.32)
Annual Change in Weight (kg) | -2.05 (-3.66, -0.45)

Metabolic acidosis (serum bicarbonate < 20 mEq/L) was observed in all topiramate-treated patients at some time in the study [see Warnings and Precautions (5.4)] . Over the whole study, 76% more topiramate-treated patients experienced persistent metabolic acidosis (i.e. 2 consecutive visits with or final serum bicarbonate < 20 mEq/L) compared to levetiracetam-treated patients. Over the whole study, 35% more topiramate-treated patients experienced a markedly abnormally low serum bicarbonate (i.e., absolute value < 17 mEq/L and ≥ 5 mEq/L decrease from pre-treatment), indicating the frequency of more severe metabolic acidosis, compared to levetiracetam-treated patients. The decrease in BMD at 12 months was correlated with decreased serum bicarbonate, suggesting that metabolic acidosis was at least a partial factor contributing to this adverse effect on BMD.

Topiramate-treated patients exhibited an increased risk for developing an increased serum creatinine and an increased serum glucose above the normal reference range compared to control patients.

Pediatric Patients Below the Age of 2 Years
Safety and effectiveness in patients below the age of 2 years have not been established for the monotherapy treatment of epilepsy.

Preventive Treatment of Migraine

Pediatric Patients 12 to 17 Years of Age

Safety and effectiveness of topiramate for the preventive treatment of migraine was studied in 5 double-blind, randomized, placebo-controlled, parallel-group trials in a total of 219 pediatric patients, at doses of 50 to 200 mg/day, or 2 to 3 mg/kg/day. These comprised a fixed dose study in 103 pediatric patients 12 to 17 years of age [see Clinical Studies (14.3)] , a flexible dose (2 to 3 mg/kg/day), placebo-controlled study in 157 pediatric patients 6 to 16 years of age (including 67 pediatric patients 12 to 16 years of age), and a total of 49 pediatric patients 12 to 17 years of age in 3 studies for the preventive treatment of migraine primarily in adults. Open-label extension phases of 3 studies enabled evaluation of long-term safety for up to 6 months after the end of the double-blind phase.

Efficacy of topiramate for the preventive treatment of migraine in pediatric patients 12 to 17 years of age is demonstrated for a 100 mg daily dose in Study 13 [see Clinical Studies (14.3)] . Efficacy of topiramate (2 to 3 mg/kg/day) for the preventive treatment of migraine was not demonstrated in a placebo-controlled trial of 157 pediatric patients (6 to 16 years of age) that included treatment of 67 pediatric patients (12 to 16 years of age) for 20 weeks.

In the pediatric trials (12 to 17 years of age) in which patients were randomized to placebo or a fixed daily dose of topiramate, the most common adverse reactions with topiramate that were seen at an incidence higher (≥5%) than in the placebo group were: paresthesia, upper respiratory tract infection, anorexia, and abdominal pain [see Adverse Reactions (6)] .

The most common cognitive adverse reaction in pooled double-blind studies in pediatric patients 12 to 17 years of age was difficulty with concentration/attention [see Warnings and Precautions (5.6)] .

Markedly abnormally low serum bicarbonate values indicative of metabolic acidosis were reported in topiramate-treated pediatric migraine patients [see Warnings and Precautions (5.4)] .

In topiramate-treated pediatric patients (12 to 17 years of age) compared to placebo-treated patients, abnormally increased results were more frequent for creatinine, BUN, uric acid, chloride, ammonia, total protein, and platelets. Abnormally decreased results were observed with topiramate vs placebo treatment for phosphorus and bicarbonate [see Clinical Trials Experience (6.1)] .

Notable changes (increases and decreases) from baseline in systolic blood pressure, diastolic blood pressure, and pulse were observed occurred more commonly in pediatric patients treated with topiramate compared to pediatric patients treated with placebo [see Clinical Pharmacology (12.2)] .

Pediatric Patients Below the Age of 12 Years

Safety and effectiveness in pediatric patients below the age of 12 years have not been established for the preventive treatment of migraine.

In a double-blind study in 90 pediatric patients 6 to 11 years of age (including 59 topiramate-treated and 31 placebo patients), the adverse reaction profile was generally similar to that seen in pooled double-blind studies of pediatric patients 12 to 17 years of age. The most common adverse reactions that occurred in topiramate -treated pediatric patients 6 to 11 years of age, and at least twice as frequently than placebo, were gastroenteritis (12% topiramate, 6% placebo), sinusitis (10% topiramate, 3% placebo), weight loss (8% topiramate, 3% placebo) and paresthesia (7% topiramate, 0% placebo). Difficulty with concentration/attention occurred in 3 topiramate-treated patients (5%) and 0 placebo-treated patients (0%).

The risk for cognitive adverse reaction was greater in younger patients (6 to 11 years of age) than in older patients (12 to 17 years of age) [see Warnings and Precautions (5.6)] .

Juvenile Animal Studies

When topiramate (0, 30, 90, and 300 mg/kg/day) was administered orally to rats during the juvenile period of development (postnatal days 12 to 50), bone growth plate thickness was reduced in males at the highest dose. The no-effect dose (90 mg/kg/day) for adverse developmental effects is approximately 2 times the maximum recommended pediatric dose (9 mg/kg/day) on a body surface area (mg/m^2) basis.

8.5 Geriatric Use

In clinical trials, 3% of patients were over age 60. No age-related differences in effectiveness or adverse effects were evident. However, clinical studies of topiramate did not include sufficient numbers of subjects age 65 and over to determine whether they respond differently than younger subjects. Dosage adjustment may be necessary for elderly with age-related renal impairment (creatinine clearance rate <70 mL/min/1.73 m^2) resulting in reduced clearance [see Dosage and Administration (2.5), Clinical Pharmacology (12.3)] .

8.6 Renal Impairment

The clearance of topiramate is reduced in patients with moderate (creatinine clearance 30 to 69 mL/min/1.73 m^2) and severe (creatinine clearance <30 mL/min/1.73 m^2) renal impairment. A dosage adjustment is recommended in patients with moderate or severe renal impairment [see Dosage and Administration (2.5), Clinical Pharmacology (12.3)] .

8.7 Patients Undergoing Hemodialysis

Topiramate is cleared by hemodialysis at a rate that is 4 to 6 times greater than in a normal individual. A dosage adjustment may be required [see Dosage and Administration (2.6), Clinical Pharmacology (12.3)] .

10 OVERDOSAGE

Overdoses of topiramate have been reported. Signs and symptoms included convulsions, drowsiness, speech disturbance, blurred vision, diplopia, impaired mentation, lethargy, abnormal coordination, stupor, hypotension, abdominal pain, agitation, dizziness and depression. The clinical consequences were not severe in most cases, but deaths have been reported after overdoses involving topiramate.

Topiramate overdose has resulted in severe metabolic acidosis [see Warnings and Precautions (5.4)] .

A patient who ingested a dose of topiramate between 96 and 110 g was admitted to a hospital with a coma lasting 20 to 24 hours followed by full recovery after 3 to 4 days.

In the event of overdose, EPRONTIA should be discontinued and general supportive treatment given until clinical toxicity has been diminished or resolved. Hemodialysis is an effective means of removing topiramate from the body.

11 DESCRIPTION

EPRONTIA (topiramate) oral solution is available as a 25 mg/mL solution for oral administration.

Topiramate has the molecular formula C12H21NO8S and a molecular weight of 339.36. Topiramate is designated chemically as 2,3:4,5-Di- O-isopropylidene-β-D-fructopyranose sulfamate and has the following structural formula:

Topiramate is a white crystalline powder with a bitter taste. Topiramate is a sulfamate-substituted monosaccharide. Topiramate is most soluble in alkaline solutions containing sodium hydroxide or sodium phosphate and having a pH of 9 to 10. It is freely soluble in acetone, chloroform, dimethylsulfoxide, and ethanol. The solubility in water is 9.8 mg/mL. Its saturated solution has a pH of 6.3.

EPRONTIA oral solution is colorless to slightly yellow colored clear viscous liquid. EPRONTIA contains the following inactive ingredients: glycerin, methylparaben, mixed berry flavor, polyethylene glycol, propylparaben, and sucralose.

12 CLINICAL PHARMACOLOGY

12.1 Mechanism of Action

The precise mechanisms by which topiramate exerts its anticonvulsant and preventive migraine effects are unknown; however, preclinical studies have revealed four properties that may contribute to topiramate's efficacy for epilepsy and the preventive treatment of migraine. Electrophysiological and biochemical evidence suggests that topiramate, at pharmacologically relevant concentrations, blocks voltage-dependent sodium channels, augments the activity of the neurotransmitter gamma-aminobutyrate at some subtypes of the GABA-A receptor, antagonizes the AMPA/kainate subtype of the glutamate receptor, and inhibits the carbonic anhydrase enzyme, particularly isozymes II and IV.

12.2 Pharmacodynamics

Topiramate has anticonvulsant activity in rat and mouse maximal electroshock seizure (MES) tests. Topiramate is only weakly effective in blocking clonic seizures induced by the GABAA receptor antagonist, pentylenetetrazole. Topiramate is also effective in rodent models of epilepsy, which include tonic and absence-like seizures in the spontaneous epileptic rat (SER) and tonic and clonic seizures induced in rats by kindling of the amygdala or by global ischemia.

Changes (increases and decreases) from baseline in vital signs (systolic blood pressure-SBP, diastolic blood pressure-DBP, pulse) occurred more frequently in pediatric patients (6 to 17 years) treated with various daily doses of topiramate (50 mg, 100 mg, 200 mg, 2 to 3 mg/kg) than in patients treated with placebo in controlled trials for the preventive treatment of migraine. The most notable changes were SBP <90 mm Hg, DBP <50 mm Hg, SBP or DBP increases or decreases ≥20 mm Hg, and pulse increases or decreases ≥30 beats per minute. These changes were often dose-related and were most frequently associated with the greatest treatment difference at the 200 mg dose level. Systematic collection of orthostatic vital signs has not been conducted. The clinical significance of these various changes in vital signs has not been clearly established.

12.3 Pharmacokinetics

Peak topiramate plasma concentrations (Cmax) occurred at approximately 0.5 hour after oral administration of EPRONTIA in healthy male subjects under fasting conditions. Oral administration of EPRONTIA with a high-fat and high calorie meal did not affect topiramate AUC0-tand AUC0-∞, but lowered the Cmaxby 28% and delayed the Tmaxby 5 hours. Overall, the impact of food-intake on topiramate pharmacokinetics is not expected to be clinically significant, and therefore, EPRONTIA can be administered without regard to food.

The pharmacokinetics of topiramate are linear with dose proportional increases in plasma concentration over the dose range studied (200 to 800 mg/day). The mean plasma elimination half-life is 21 hours after single or multiple doses. Steady-state is thus reached in about 4 days in patients with normal renal function. Topiramate is 15% to 41% bound to human plasma proteins over the blood concentration range of 0.5 to 250 μg/mL. The fraction bound decreased as blood concentration increased.

Carbamazepine and phenytoin do not alter the binding of topiramate. Sodium valproate, at 500 μg/mL (a concentration 5 to 10 times higher than considered therapeutic for valproate) decreased the protein binding of topiramate from 23% to 13%. Topiramate does not influence the binding of sodium valproate.

Metabolism and Excretion

Topiramate is not extensively metabolized and is primarily eliminated unchanged in the urine (approximately 70% of an administered dose). Six metabolites have been identified in humans, none of which constitutes more than 5% of an administered dose. The metabolites are formed via hydroxylation, hydrolysis, and glucuronidation. There is evidence of renal tubular reabsorption of topiramate. In rats, given probenecid to inhibit tubular reabsorption, along with topiramate, a significant increase in renal clearance of topiramate was observed. This interaction has not been evaluated in humans. Overall, oral plasma clearance (CL/F) is approximately 20 to 30 mL/min in adults following oral administration.

Specific Populations

Renal Impairment

The clearance of topiramate was reduced by 42% in subjects with moderate renal impairment (creatinine clearance 30 to 69 mL/min/1.73 m^2) and by 54% in subjects with severe renal impairment (creatinine clearance <30 mL/min/1.73 m^2) compared to subjects with normal renal function (creatinine clearance >70 mL/min/1.73 m^2) [see Dosage and Administration (2.4) and (2.5)] .

Hemodialysis

Topiramate is cleared by hemodialysis. Using a high-efficiency, counterflow, single pass-dialysate hemodialysis procedure, topiramate dialysis clearance was 120 mL/min with blood flow through the dialyzer at 400 mL/min. This high clearance (compared to 20 to 30 mL/min total oral clearance in healthy adults) will remove a clinically significant amount of topiramate from the patient over the hemodialysis treatment period [see Dosage and Administration (2.6), Use in Specific Populations (8.7)] .

Hepatic Impairment

Plasma clearance of topiramate decreased a mean of 26% in patients with moderate to severe hepatic impairment.

Age, Gender, and Race

The pharmacokinetics of topiramate in elderly subjects (65 to 85 years of age, N=16) were evaluated in a controlled clinical study. The elderly subject population had reduced renal function (creatinine clearance [-20%]) compared to young adults. Following a single oral 100 mg dose, maximum plasma concentration for elderly and young adults was achieved at approximately 1 to 2 hours. Reflecting the primary renal elimination of topiramate, topiramate plasma and renal clearance were reduced 21% and 19%, respectively, in elderly subjects, compared to young adults. Similarly, topiramate half-life was longer (13%) in the elderly. Reduced topiramate clearance resulted in slightly higher maximum plasma concentration (23%) and AUC (25%) in elderly subjects than observed in young adults. Topiramate clearance is decreased in the elderly only to the extent that renal function is reduced [see Dosage and Administration (2.4) and Use in Specific Populations (8.5)] .

Clearance of topiramate in adults was not affected by gender or race.

Pediatric Pharmacokinetics

Pharmacokinetics of topiramate were evaluated in patients age 2 to <16 years. Patients received either no or a combination of other antiepileptic drugs. A population pharmacokinetic model was developed on the basis of pharmacokinetic data from relevant topiramate clinical studies. This dataset contained data from 1217 subjects including 258 pediatric patients age 2 to <16 years (95 pediatric patients <10 years of age).

Pediatric patients on adjunctive treatment exhibited a higher oral clearance (L/h) of topiramate compared to patients on monotherapy, presumably because of increased clearance from concomitant enzyme-inducing antiepileptic drugs. In comparison, topiramate clearance per kg is greater in pediatric patients than in adults and in young pediatric patients (down to 2 years) than in older pediatric patients. Consequently, the plasma drug concentration for the same mg/kg/day dose would be lower in pediatric patients compared to adults and also in younger pediatric patients compared to older pediatric patients. Clearance was independent of dose.

As in adults, hepatic enzyme-inducing antiepileptic drugs decrease the steady state plasma concentrations of topiramate.

Pediatric Patients with Obesity

A population PK analysis of topiramate was conducted in 129 children <21 years of age with and without obesity to evaluate the potential impact of obesity on plasma topiramate exposures. Obesity was defined as BMI ≥ 95th percentile for age and sex based on CDC-recommended BMI-for-age growth charts for males and females. Using the currently recommended dosing regimens, children with obesity are likely to have median values of average concentration at steady-state and trough concentration at steady-state that are up to 20% lower, and 19% lower, respectively, compared to children without obesity. Dosage adjustment according to obesity status is not necessary.

Drug Interactions

In vitrostudies indicate that topiramate does not inhibit CYP1A2, CYP2A6, CYP2B6, CYP2C9, CYP2D6, CYP2E1, or CYP3A4/5 isozymes. In vitrostudies indicate that topiramate is a mild inhibitor of CYP2C19 and a mild inducer of CYP3A4.

Antiepileptic Drugs

Potential interactions between topiramate and standard AEDs were assessed in controlled clinical pharmacokinetic studies in patients with epilepsy. The effects of these interactions on mean plasma AUCs are summarized in Table 11.

In Table 11, the second column (AED concentration) describes what happens to the concentration of the co-administered AED listed in the first column when topiramate is added. The third column (topiramate concentration) describes how the co-administration of a drug listed in the first column modifies the concentration of topiramate when compared to topiramate given alone.

Table 11: Summary of AED Interactions with Topiramate
AED Co-administered | AED Concentration | Topiramate Concentration
Phenytoin | NC or 25% increase [Plasma concentration increased 25% in some patients, generally those on a twice a day dosing regimen of phenytoin.] | 48% decrease
Carbamazepine (CBZ) | NC | 40% decrease
CBZ epoxide [Is not administered but is an active metabolite of carbamazepine.] | NC | NE
Valproic acid | 11% decrease | 14% decrease
Phenobarbital | NC | NE
Primidone | NC | NE
Lamotrigine | NC at TPM doses up to 400 mg/day | 13% decrease
NC = Less than 10% change in plasma concentration.; AED = Antiepileptic drug.; NE = Not Evaluated.; TPM = Topiramate

Oral Contraceptives

In a pharmacokinetic interaction study in healthy volunteers with a concomitantly administered combination oral contraceptive product containing 1 mg norethindrone (NET) plus 35 mcg ethinyl estradiol (EE), topiramate, given in the absence of other medications at doses of 50 to 200 mg/day, was not associated with statistically significant changes in mean exposure (AUC) to either component of the oral contraceptive. In another study, exposure to EE was statistically significantly decreased at doses of 200, 400, and 800 mg/day (18%, 21%, and 30%, respectively) when given as adjunctive therapy in patients taking valproic acid. In both studies, topiramate (50 mg/day to 800 mg/day) did not significantly affect exposure to NET and there was no significant dose-dependent change in EE exposure for doses of 50 to 200 mg/day. The clinical significance of the changes observed is not known [see Drug Interactions (7.4)] .

Digoxin

In a single-dose study, serum digoxin AUC was decreased by 12% with concomitant topiramate administration. The clinical relevance of this observation has not been established.

Hydrochlorothiazide

A drug interaction study conducted in healthy volunteers evaluated the steady-state pharmacokinetics of hydrochlorothiazide (HCTZ) (25 mg every 24 hours) and topiramate (96 mg every 12 hours) when administered alone and concomitantly. The results of this study indicate that topiramate Cmaxincreased by 27% and AUC increased by 29% when HCTZ was added to topiramate. The clinical significance of this change is unknown. The steady-state pharmacokinetics of HCTZ were not significantly influenced by the concomitant administration of topiramate. Clinical laboratory results indicated decreases in serum potassium after topiramate or HCTZ administration, which were greater when HCTZ and topiramate were administered in combination.

Metformin

A drug interaction study conducted in healthy volunteers evaluated the steady-state pharmacokinetics of metformin (500 mg every 12 hours) and topiramate in plasma when metformin was given alone and when metformin and topiramate (100 mg every 12 hours) were given simultaneously. The results of this study indicated that the mean metformin Cmaxand AUC0-12hincreased by 18% and 25%, respectively, when topiramate was added. Topiramate did not affect metformin tmax. The clinical significance of the effect of topiramate on metformin pharmacokinetics is not known. Oral plasma clearance of topiramate appears to be reduced when administered with metformin. The clinical significance of the effect of metformin on topiramate pharmacokinetics is unclear.

Pioglitazone

A drug interaction study conducted in healthy volunteers evaluated the steady-state pharmacokinetics of topiramate and pioglitazone when administered alone and concomitantly. A 15% decrease in the AUCt,ssof pioglitazone with no alteration in Cmax,sswas observed. This finding was not statistically significant. In addition, a 13% and 16% decrease in Cmax,ssand AUCt,ssrespectively, of the active hydroxy-metabolite was noted as well as a 60% decrease in Cmax,ssand AUCt,ssof the active keto-metabolite. The clinical significance of these findings is not known.

Glyburide

A drug-drug interaction study conducted in patients with type 2 diabetes evaluated the steady-state pharmacokinetics of glyburide (5 mg/day) alone and concomitantly with topiramate (150 mg/day). There was a 22% decrease in Cmaxand a 25% reduction in AUC24for glyburide during topiramate administration. Systemic exposure (AUC) of the active metabolites, 4- trans-hydroxy-glyburide (M1) and 3- cis-hydroxyglyburide (M2), was also reduced by 13% and 15%, and Cmaxwas reduced by 18% and 25%, respectively. The steady-state pharmacokinetics of topiramate were unaffected by concomitant administration of glyburide.

Lithium

In patients, the pharmacokinetics of lithium were unaffected during treatment with topiramate at doses of 200 mg/day; however, there was an observed increase in systemic exposure of lithium (27% for Cmaxand 26% for AUC) following topiramate doses up to 600 mg/day [see Drug Interactions (7.7)] .

Haloperidol

The pharmacokinetics of a single dose of haloperidol (5 mg) were not affected following multiple dosing of topiramate (100 mg every 12 hr) in 13 healthy adults (6 males, 7 females).

Amitriptyline

There was a 12% increase in AUC and Cmaxfor amitriptyline (25 mg per day) in 18 healthy subjects (9 males, 9 females) receiving 200 mg/day of topiramate.

Sumatriptan

Multiple dosing of topiramate (100 mg every 12 hours) in 24 healthy volunteers (14 males, 10 females) did not affect the pharmacokinetics of single-dose sumatriptan either orally (100 mg) or subcutaneously (6 mg).

Risperidone

When administered concomitantly with topiramate at escalating doses of 100, 250, and 400 mg/day, there was a reduction in risperidone systemic exposure (16% and 33% for steady-state AUC at the 250 and 400 mg/day doses of topiramate). No alterations of 9-hydroxyrisperidone levels were observed. Co-administration of topiramate 400 mg/day with risperidone resulted in a 14% increase in Cmaxand a 12% increase in AUC12of topiramate. There were no clinically significant changes in the systemic exposure of risperidone plus 9-hydroxyrisperidone or of topiramate; therefore, this interaction is not likely to be of clinical significance.

Propranolol

Multiple dosing of topiramate (200 mg/day) in 34 healthy volunteers (17 males, 17 females) did not affect the pharmacokinetics of propranolol following daily 160 mg doses. Propranolol doses of 160 mg/day in 39 volunteers (27 males, 12 females) had no effect on the exposure to topiramate, at a dose of 200 mg/day of topiramate.

Dihydroergotamine

Multiple dosing of topiramate (200 mg/day) in 24 healthy volunteers (12 males, 12 females) did not affect the pharmacokinetics of a 1 mg subcutaneous dose of dihydroergotamine. Similarly, a 1 mg subcutaneous dose of dihydroergotamine did not affect the pharmacokinetics of a 200 mg/day dose of topiramate in the same study.

Diltiazem

Co-administration of diltiazem (240 mg Cardizem CD®) with topiramate (150 mg/day) resulted in a 10% decrease in Cmaxand a 25% decrease in diltiazem AUC, a 27% decrease in Cmaxand an 18% decrease in des-acetyl diltiazem AUC, and no effect on N-desmethyl diltiazem. Co-administration of topiramate with diltiazem resulted in a 16% increase in Cmaxand a 19% increase in AUC12of topiramate.

Venlafaxine

Multiple dosing of topiramate (150 mg/day) in healthy volunteers did not affect the pharmacokinetics of venlafaxine or O-desmethyl venlafaxine. Multiple dosing of venlafaxine (150 mg) did not affect the pharmacokinetics of topiramate.

13 NONCLINICAL TOXICOLOGY

13.1 Carcinogenesis, Mutagenesis, Impairment of Fertility

Carcinogenesis

An increase in urinary bladder tumors was observed in mice given topiramate (0, 20, 75, and 300 mg/kg/day) in the diet for 21 months. The increase in the incidence of bladder tumors in males and females receiving 300 mg/kg/day was primarily due to the increased occurrence of a smooth muscle tumor considered histomorphologically unique to mice. The higher of the doses not associated with an increase in tumors (75 mg/kg/day) is equivalent to the maximum recommended human dose (MRHD) for epilepsy (400 mg), and approximately 4 times the MRHD for migraine (100 mg) on a mg/m^2basis. The relevance of this finding to human carcinogenic risk is uncertain. No evidence of carcinogenicity was seen in rats following oral administration of topiramate for 2 years at doses up to 120 mg/kg/day (approximately 3 times the MRHD for epilepsy and 12 times the MRHD for migraine on a mg/m^2basis).

Mutagenesis

Topiramate did not demonstrate genotoxic potential when tested in a battery of in vitroand in vivoassays. Topiramate was not mutagenic in the Ames test or the in vitromouse lymphoma assay; it did not increase unscheduled DNA synthesis in rat hepatocytes in vitro; and it did not increase chromosomal aberrations in human lymphocytes in vitroor in rat bone marrow in vivo.

Impairment of Fertility

No adverse effects on male or female fertility were observed in rats administered topiramate orally at doses up to 100 mg/kg/day (2.5 times the MRHD for epilepsy and 10 times the MRHD for migraine on a mg/m^2basis) prior to and during mating and early pregnancy.

14 CLINICAL STUDIES

The safety and efficacy of EPRONTIA are based on the relative bioavailability of EPRONTIA compared to topiramate sprinkle capsules in healthy subjects [see Clinical Pharmacology (12.3)] . Topiramate sprinkle capsules have comparable bioavailability to topiramate tablets.

The studies described in the following subsections were conducted using topiramate tablets or sprinkle capsules.

14.1 Monotherapy Epilepsy

Patients with Partial-Onset or Primary Generalized Tonic-Clonic Seizures

Adults and Pediatric Patients 10 Years of Age and Older

The effectiveness of topiramate as initial monotherapy in adults and pediatric patients 10 years of age and older with partial-onset or primary generalized tonic-clonic seizures was established in a multicenter, randomized, double-blind, parallel-group trial (Study 1).

Study 1 was conducted in 487 patients diagnosed with epilepsy (6 to 83 years of age) who had 1 or 2 well-documented seizures during the 3-month retrospective baseline phase who then entered the study and received topiramate 25 mg/day for 7 days in an open-label fashion. Forty-nine percent of patients had no prior AED treatment and 17% had a diagnosis of epilepsy for greater than 24 months. Any AED therapy used for temporary or emergency purposes was discontinued prior to randomization. In the double-blind phase, 470 patients were randomized to titrate up to 50 mg/day or 400 mg/day. If the target dose could not be achieved, patients were maintained on the maximum tolerated dose. Fifty-eight percent of patients achieved the maximal dose of 400 mg/day for >2 weeks, and patients who did not tolerate 150 mg/day were discontinued.

The primary efficacy assessment was a between-group comparison of time to first seizure during the double-blind phase. Comparison of the Kaplan-Meier survival curves of time to first seizure favored the topiramate 400 mg/day group over the topiramate 50 mg/day group (Figure 1). The treatment effects with respect to time to first seizure were consistent across various patient subgroups defined by age, sex, geographic region, baseline body weight, baseline seizure type, time since diagnosis, and baseline AED use.

Figure 1: Kaplan-Meier Estimates of Cumulative Rates for Time to First Seizure in Study 1

Pediatric Patients 2 to 9 Years of Age

The conclusion that topiramate is effective as initial monotherapy in pediatric patients 2 to 9 years of age with partial-onset or primary generalized tonic-clonic seizures was based on a pharmacometric bridging approach using data from the controlled epilepsy trials described in labeling. This approach consisted of first showing a similar exposure-response relationship between pediatric patients down to 2 years of age and adults when topiramate was given as adjunctive therapy. Similarity of exposure response was also demonstrated in pediatric patients 6 to less than 16 years of age and adults when topiramate was given as initial monotherapy. Specific dosing in pediatric patients 2 to 9 years of age was derived from simulations utilizing plasma exposure ranges observed in pediatric and adult patients treated with topiramate initial monotherapy [see Dosage and Administration (2.1)] .

14.2 Adjunctive Therapy Epilepsy

Adult Patients with Partial-Onset Seizures

The effectiveness of topiramate as an adjunctive treatment for adults with partial-onset seizures was established in six multicenter, randomized, double-blind, placebo-controlled trials (Studies 2, 3, 4, 5, 6, and 7), two comparing several dosages of topiramate and placebo and four comparing a single dosage with placebo, in patients with a history of partial-onset seizures, with or without secondarily generalized seizures.

Patients in these studies were permitted a maximum of two antiepileptic drugs (AEDs) in addition to topiramate tablets or placebo. In each study, patients were stabilized on optimum dosages of their concomitant AEDs during baseline phase lasting between 4 and 12 weeks. Patients who experienced a pre-specified minimum number of partial-onset seizures, with or without secondary generalization, during the baseline phase (12 seizures for 12-week baseline, 8 for 8-week baseline or 3 for 4-week baseline) were randomly assigned to placebo or a specified dose of topiramate tablets in addition to their other AEDs.

Following randomization, patients began the double-blind phase of treatment. In five of the six studies, patients received active drug beginning at 100 mg per day; the dose was then increased by 100 mg or 200 mg/day increments weekly or every other week until the assigned dose was reached, unless intolerance prevented increases. In the sixth study (Study 7), the 25 or 50 mg/day initial doses of topiramate were followed by respective weekly increments of 25 or 50 mg/day until the target dose of 200 mg/day was reached. After titration, patients entered a 4, 8 or 12-week stabilization period. The numbers of patients randomized to each dose and the actual mean and median doses in the stabilization period are shown in Table 12.

Pediatric Patients 2 to 16 Years of Age with Partial-Onset Seizures

The effectiveness of topiramate as an adjunctive treatment for pediatric patients 2 to 16 years of age with partial-onset seizures was established in a multicenter, randomized, double-blind, placebo-controlled trial (Study 8), comparing topiramate and placebo in patients with a history of partial-onset seizures, with or without secondarily generalized seizures (see Table 13).

Patients in this study were permitted a maximum of two antiepileptic drugs (AEDs) in addition to topiramate tablets or placebo. In this study, patients were stabilized on optimum dosages of their concomitant AEDs during an 8-week baseline phase. Patients who experienced at least six partial-onset seizures, with or without secondarily generalized seizures, during the baseline phase were randomly assigned to placebo or topiramate tablets in addition to their other AEDs.

Following randomization, patients began the double-blind phase of treatment. Patients received active drug beginning at 25 or 50 mg/day; the dose was then increased by 25 mg to 150 mg/day increments every other week until the assigned dosage of 125, 175, 225, or 400 mg/day based on patients' weight to approximate a dosage of 6 mg/kg/day was reached, unless intolerance prevented increases. After titration, patients entered an 8-week stabilization period.

Patients With Primary Generalized Tonic-Clonic Seizures

The effectiveness of topiramate as an adjunctive treatment for primary generalized tonic-clonic seizures in patients 2 years of age and older was established in a multicenter, randomized, double-blind, placebo-controlled trial (Study 9), comparing a single dosage of topiramate and placebo (see Table 13).

Patients in Study 9 were permitted a maximum of two antiepileptic drugs (AEDs) in addition to topiramate or placebo. Patients were stabilized on optimum dosages of their concomitant AEDs during an 8-week baseline phase. Patients who experienced at least three primary generalized tonic-clonic seizures during the baseline phase were randomly assigned to placebo or topiramate in addition to their other AEDs.

Following randomization, patients began the double-blind phase of treatment. Patients received active drug beginning at 50 mg/day for four weeks; the dose was then increased by 50 mg to 150 mg/day increments every other week until the assigned dose of 175, 225, or 400 mg/day based on patients' body weight to approximate a dosage of 6 mg/kg/day was reached, unless intolerance prevented increases. After titration, patients entered a 12-week stabilization period.

Patients With Lennox-Gastaut Syndrome

The effectiveness of topiramate as an adjunctive treatment for seizures associated with Lennox- Gastaut syndrome was established in a multicenter, randomized, double-blind, placebo-controlled trial (Study 10) comparing a single dosage of topiramate with placebo in patients 2 years of age and older (see Table 13).

Patients in Study 10 were permitted a maximum of two antiepileptic drugs (AEDs) in addition to topiramate or placebo. Patients who were experiencing at least 60 seizures per month before study entry were stabilized on optimum dosages of their concomitant AEDs during a 4-week baseline phase. Following baseline, patients were randomly assigned to placebo or topiramate in addition to their other AEDs. Active drug was titrated beginning at 1 mg/kg/day for a week; the dose was then increased to 3 mg/kg/day for one week, then to 6 mg/kg/day. After titration, patients entered an 8-week stabilization period.

The primary measures of effectiveness were the percent reduction in drop attacks and a parental global rating of seizure severity.

Table 12: Topiramate Dose Summary During the Stabilization Periods of Each of Six Double-Blind, Placebo-Controlled, Adjunctive Trials in Adults with Partial-Onset Seizures [Dose-response studies were not conducted for other indications or pediatric partial-onset seizures.]
Study | Stabilization Dose | Placebo [Placebo dosages are given as the number of tablets. Placebo target dosages were as follows: Protocol 3 4 tablets/day; Protocols 1 and 4, 6 tablets/day; Protocols 5 and 6, 8 tablets/day; Protocol 2, 10 tablets/day.] | Target TOPIRAMATE Dosage (mg/day)
Study | Stabilization Dose | Placebo [Placebo dosages are given as the number of tablets. Placebo target dosages were as follows: Protocol 3 4 tablets/day; Protocols 1 and 4, 6 tablets/day; Protocols 5 and 6, 8 tablets/day; Protocol 2, 10 tablets/day.] | 200 | 400 | 600 | 800 | 1,000
2 | N; Mean Dose; Median Dose | 42; 5.9; 6.0 | 42; 200; 200 | 40; 390; 400 | 41; 556; 600 | -- | --
3 | N; Mean Dose; Median Dose | 44; 9.7; 10.0 | -- | -- | 40; 544; 600 | 45; 739; 800 | 40; 796; 1,000
4 | N; Mean Dose; Median Dose | 23; 3.8; 4.0 | -- | 19; 395; 400 | -- | -- | --
5 | N; Mean Dose; Median Dose | 30; 5.7; 6.0 | -- | -- | 28; 522; 600 | -- | --
6 | N; Mean Dose; Median Dose | 28; 7.9; 8.0 | -- | -- | -- | 25; 568; 600 | --
7 | N; Mean Dose; Median Dose | 90; 8; 8 | 157; 200; 200 | -- | -- | -- | --

In all adjunctive trials, the reduction in seizure rate from baseline during the entire double-blind phase was measured. The median percent reductions in seizure rates and the responder rates (fraction of patients with at least a 50% reduction) by treatment group for each study are shown below in Table 13. As described above, a global improvement in seizure severity was also assessed in the Lennox-Gastaut trial.

Table 13: Efficacy Results in Double-Blind, Placebo-Controlled, Adjunctive Epilepsy Trials
Study# | # | Target TOPIRAMATE Dosage (mg per day)
Study# | # | Placebo | 200 | 400 | 600 | 800 | 1,000 | ≈6mg/kg/day [For Studies 8 and 9, specified target dosages (<9.3 mg/kg/day) were assigned based on subject's weight to approximate a dosage of 6mg/kg per day; these dosages corresponded to mg/day dosages of 125, 175, 225, and 400 mg/day.]
Partial-Onset Seizures Studies in Adults
2 | N | 45 | 45 | 45 | 46 | -- | -- | --
 | Median % Reduction | 12 | 27a | 48b | 45c | -- | -- | --
 | % Responders | 18 | 24 | 44d | 46d | -- | -- | --
3 | N | 47 | -- | -- | 48 | 48 | 47 | --
 | Median % Reduction | 2 | -- | -- | 41c | 41c | 36c
 | % Responders | 9 | -- | -- | 40c | 41c | 36d
4 | N | 24 | -- | 23 | -- | -- | -- | --
 | Median % Reduction | 1 | -- | 41e | -- | -- | -- | --
 | % Responders | 8 | -- | 35d | -- | -- | -- | --
5 | N | 30 | -- | -- | 30 | -- | -- | --
 | Median % Reduction | -12 | -- | -- | 46f | -- | -- | --
 | % Responders | 10 | -- | -- | 47c | -- | -- | --
6 | N | 28 | -- | -- | -- | 28 | -- | --
 | Median % Reduction | -21 | -- | -- | -- | 24c | -- | --
 | % Responders | 0 | -- | -- | -- | 43c | -- | --
7 | N | 91 | 168 | -- | -- | -- | -- | --
 | Median % Reduction | 20 | 44c | -- | -- | -- | -- | --
 | % Responders | 24 | 45c
Partial-Onset Seizures Studies in Pediatric Patients
8 | N | 45 | -- | -- | -- | -- | -- | 41
 | Median % Reduction | 11 | -- | -- | -- | -- | -- | 33d
 | % Responders | 20 | -- | -- | -- | -- | -- | 39
Primary Generalized Tonic-Clonich
9 | N | 40 | -- | -- | -- | -- | -- | 39
 | Median % Reduction | 9 | -- | -- | -- | -- | -- | 57d
 | % Responders | 20 | -- | -- | -- | -- | -- | 56c
Lennox-Gastaut Syndromei
10 | N | 49 | -- | -- | -- | -- | -- | 46
 | Median % Reduction | -5 | -- | -- | -- | -- | -- | 15d
 | % Responders | 14 |  |  |  |  |  | 28g
 | Improvement in Seizure Severityj | 28 |  |  |  |  |  | 52d
Comparisons with placebo:ap=0.080;bp ≤ 0.010;cp ≤ 0.001;dp ≤ 0.050;ep=0.065;fp≤0.005;gp=0.071;
hMedian % reduction and % responders are reported for PGTC seizures;
iMedian % reduction and % responders for drop attacks, i.e., tonic or atonic seizures;
jPercentage of subjects who were minimally, much, or very much improved from baseline.

Subset analyses of the antiepileptic efficacy of topiramate tablets in these studies showed no differences as a function of gender, race, age, baseline seizure rate, or concomitant AED.

In clinical trials for epilepsy, daily dosages were decreased in weekly intervals by 50 to 100 mg/day in adults and over a 2- to 8-week period in pediatric patients; transition was permitted to a new antiepileptic regimen when clinically indicated.

14.3 Preventive Treatment of Migraine

Adult Patients

The results of 2 multicenter, randomized, double-blind, placebo-controlled, parallel-group clinical trials established the effectiveness of topiramate in the preventive treatment of migraine. The design of both trials (Study 11 was conducted in the U.S. and Study 12 was conducted in the U.S. and Canada) was identical, enrolling patients with a history of migraine, with or without aura, for at least 6 months, according to the International Headache Society (IHS) diagnostic criteria. Patients with a history of cluster headaches or basilar, ophthalmoplegic, hemiplegic, or transformed migraine headaches were excluded from the trials. Patients were required to have completed up to a 2-week washout of any prior migraine preventive medications before starting the baseline phase.

Patients who experienced 3 to 12 migraine headaches over the 4 weeks in the baseline phase were randomized to either topiramate 50 mg/day, 100 mg/day, 200 mg/day, or placebo and treated for a total of 26 weeks (8-week titration period and 18-week maintenance period). Treatment was initiated at 25 mg/day for one week, and then the daily dosage was increased by 25 mg increments each week until reaching the assigned target dose or maximum tolerated dose (administered twice daily).

Effectiveness of treatment was assessed by the reduction in migraine headache frequency, as measured by the change in 4-week migraine rate (according to migraines classified by IHS criteria) from the baseline phase to double-blind treatment period in each topiramate treatment group compared to placebo in the Intent-To-Treat (ITT) population.

In Study 11, a total of 469 patients (416 females, 53 males), ranging in age from 13 to 70 years, were randomized and provided efficacy data. Two hundred sixty-five patients completed the entire 26-week double-blind phase. The median average daily dosages were 48 mg/day, 88 mg/day, and 132 mg/day in the target dose groups of topiramate 50, 100, and 200 mg/day, respectively.

The mean migraine headache frequency rate at baseline was approximately 5.5 migraine headaches/28 days and was similar across treatment groups. The change in the mean 4-week migraine headache frequency from baseline to the double-blind phase was -1.3, -2.1, and -2.2 in the topiramate 50, 100, and 200 mg/day groups, respectively, versus -0.8 in the placebo group (see Figure 2). The treatment differences between the topiramate 100 and 200 mg/day groups versus placebo were similar and statistically significant (p<0.001 for both comparisons).

In Study 12, a total of 468 patients (406 females, 62 males), ranging in age from 12 to 65 years, were randomized and provided efficacy data. Two hundred fifty-five patients completed the entire 26-week double-blind phase. The median average daily dosages were 47 mg/day, 86 mg/day, and 150 mg/day in the target dose groups of topiramate 50, 100, and 200 mg/day, respectively.

The mean migraine headache frequency rate at baseline was approximately 5.5 migraine headaches/28 days and was similar across treatment groups. The change in the mean 4-week migraine headache period frequency from baseline to the double-blind phase was -1.4, -2.1, and -2.4 in the topiramate 50, 100, and 200 mg/day groups, respectively, versus -1.1 in the placebo group (see Figure 2). The differences between the topiramate 100 and 200 mg/day groups versus placebo were similar and statistically significant (p=0.008 and p <0.001, respectively).

In both studies, there were no apparent differences in treatment effect within age or gender subgroups. Because most patients were Caucasian, there were insufficient numbers of patients from different races to make a meaningful comparison of race.

For patients withdrawing from topiramate, daily dosages were decreased in weekly intervals by 25 to 50 mg/day.

Figure 2: Reduction in 4-Week Migraine Headache Frequency

(Studies 11 and 12 for Adults and Adolescents)

Pediatric Patients 12 to 17 Years of Age

The effectiveness of topiramate for the preventive treatment of migraine in pediatric patients 12 to 17 years of age was established in a multicenter, randomized, double-blind, parallel-group trial (Study 13). The study enrolled 103 patients (40 male, 63 female) 12 to 17 years of age with episodic migraine headaches with or without aura. Patient selection was based on IHS criteria for migraines (using proposed revisions to the 1988 IHS pediatric migraine criteria [IHS-R criteria]).

Patients who experienced 3 to 12 migraine attacks (according to migraines classified by patient reported diaries) and ≤14 headache days (migraine and non-migraine) during the 4-week prospective baseline period were randomized to either topiramate 50 mg/day, 100 mg/day, or placebo and treated for a total of 16 weeks (4-week titration period followed by a 12-week maintenance period). Treatment was initiated at 25 mg/day for one week, and then the daily dosage was increased by 25 mg increments each week until reaching the assigned target dose or maximum tolerated dose (administered twice daily). Approximately 80% or more patients in each treatment group completed the study. The median average daily dosages were 45 and 79 mg/day in the target dose groups of topiramate 50 and 100 mg/day, respectively.

Effectiveness of treatment was assessed by comparing each topiramate treatment group to placebo (ITT population) for the percent reduction from baseline to the last 12 weeks of the double-blind phase in the monthly migraine attack rate (primary endpoint). The percent reduction from baseline to the last 12 weeks of the double-blind phase in average monthly migraine attack rate is shown in Table 14.

The 100 mg topiramate dose produced a statistically significant treatment difference relative to placebo of 28% reduction from baseline in the monthly migraine attack rate.

The mean reduction from baseline to the last 12 weeks of the double-blind phase in average monthly attack rate, a key secondary efficacy endpoint in Study 13 (and the primary efficacy endpoint in Studies 11 and 12, of adults) was 3.0 for 100 mg topiramate dose and 1.7 for placebo. This 1.3 treatment difference in mean reduction from baseline of monthly migraine rate was statistically significant (p = 0.0087).

Table 14: Percent Reduction from Baseline to the Last 12 Weeks of Double-Blind Phase in Average Monthly Attack Rate: Study 13 (Intent-to-Treat Analysis Set)
Category | Placebo (N=33) | TOPIRAMATE 50 mg/day (N=35) | TOPIRAMATE 100 mg/day (N=35)
Baseline
Median | 3.6 | 4.0 | 4.0
Last 12 Weeks of Double-Blind Phase
Median | 2.3 | 2.3 | 1.0
Percent Reduction (%)
Median | 44.4 | 44.6 | 72.2
P-value vs. Placebo [P-values (two-sided) for comparisons relative to placebo are generated by applying an ANCOVA model on ranks that includes subject's stratified age at baseline, treatment group, and analysis center as factors and monthly migraine attack rate during baseline period as a covariate.] , [P-values for the dose groups are the adjusted p-value according to the Hochberg multiple comparison procedure.] |  | 0.7975 | 0.0164 [Indicates p-value is <0.05 (two-sided).]

16 HOW SUPPLIED/STORAGE AND HANDLING

16.1 How Supplied

EPRONTIA oral solution 25 mg/mL is supplied as a colorless to slightly yellow colored clear viscous liquid in white HDPE bottles. It is available as follows:

NDC | Size
NDC 52652-9001-3 | 120 mL
NDC 52652-9001-2 | 240 mL
NDC 52652-9001-1 | 473 mL

16.2 Storage and Handling

EPRONTIA is stored at 20°C to 25°C (68°F to 77°F); excursions permitted between 15°C to 30°C (59° to 86°F) [see USP Controlled Room Temperature]. Discard unused portion 90 days after first opening.

17 PATIENT COUNSELING INFORMATION

Advise the patient to read the FDA-approved patient labeling (Medication Guide).

Eye Disorders

Instruct patients taking EPRONTIA to seek immediate medical attention if they experience blurred vision, visual disturbances, or periorbital pain [see Warnings and Precautions (5.1, 5.2)] .

Oligohidrosis and Hyperthermia

Closely monitor EPRONTIA treated patients, especially pediatric patients, for evidence of decreased sweating and increased body temperature, especially in hot weather. Counsel patients to contact their healthcare professionals immediately if they develop a high or persistent fever, or decreased sweating [see Warnings and Precautions (5.3)] .

Metabolic Acidosis

Warn patients about the potential significant risk for metabolic acidosis that may be asymptomatic and may be associated with adverse effects on kidneys (e.g., kidney stones, nephrocalcinosis), bones (e.g., osteoporosis, osteomalacia, and/or rickets in children), and growth (e.g., growth delay/retardation) in pediatric patients, and on the fetus [see Warnings and Precautions (5.4), Use in Specific Populations (8.1)] .

Suicidal Behavior and Ideation

Counsel patients, their caregivers, and families that AEDs, including EPRONTIA, may increase the risk of suicidal thoughts and behavior, and advise of the need to be alert for the emergence or worsening of the signs and symptoms of depression, any unusual changes in mood or behavior or the emergence of suicidal thoughts, or behavior or thoughts about self-harm. Instruct patients to immediately report behaviors of concern to their healthcare providers [see Warnings and Precautions (5.5)] .

Interference with Cognitive and Motor Performance

Warn patients about the potential for somnolence, dizziness, confusion, difficulty concentrating, or visual effects, and advise patients not to drive or operate machinery until they have gained sufficient experience on EPRONTIA to gauge whether it adversely affects their mental performance, motor performance, and/or vision [see Warnings and Precautions (5.6)] .

Even when taking EPRONTIA or other anticonvulsants, some patients with epilepsy will continue to have unpredictable seizures. Therefore, advise all patients taking EPRONTIA for epilepsy to exercise appropriate caution when engaging in any activities where loss of consciousness could result in serious danger to themselves or those around them (including swimming, driving a car, climbing in high places, etc.). Some patients with refractory epilepsy will need to avoid such activities altogether. Discuss the appropriate level of caution with patients before patients with epilepsy engage in such activities.

Fetal Toxicity

Inform pregnant women and women of childbearing potential that use of EPRONTIA during pregnancy can cause fetal harm. EPRONTIA increases the risk of major congenital malformations, including but not limited to cleft lip and/or cleft palate (oral clefts), which occur early in pregnancy before many women know they are pregnant. Also inform patients that infants exposed to topiramate monotherapy in uteromay be SGA [see Use in Specific Populations (8.1)] . There may also be risks to the fetus from chronic metabolic acidosis with use of EPRONTIA during pregnancy [see Warnings and Precautions (5.7), Use in Specific Populations (8.1)] . When appropriate, counsel pregnant women and women of childbearing potential about alternative therapeutic options.

Advise women of childbearing potential who are not planning a pregnancy to use effective contraception while using EPRONTIA, keeping in mind that there is a potential for decreased contraceptive efficacy when using estrogen-containing or progestin-only contraceptives with topiramate [see Drug Interactions (7.4)] .

Encourage pregnant women using EPRONTIA, to enroll in the North American Antiepileptic Drug (NAAED) Pregnancy Registry. The registry is collecting information about the safety of antiepileptic drugs during pregnancy [see Use in Specific Populations (8.1)] .

Decrease in Bone Mineral Density

Inform the patient or caregiver that long-term treatment with EPRONTIA can decrease bone formation and increase bone resorption in children [see Warnings and Precautions (5.9)].

Negative Effects on Growth (Height and Weight)

Discuss with the patient or caregiver that long-term EPRONTIA treatment may attenuate growth as reflected by slower height increase and weight gain in pediatric patients [see Warnings and Precautions (5.10)].

Serious Skin Reactions

Inform patients about the signs of serious skin reactions. Instruct patients to immediately inform their healthcare provider at the first appearance of skin rash [see Warnings and Precautions (5.11)].

Hyperammonemia and Encephalopathy

Warn patients about the possible development of hyperammonemia with or without encephalopathy. Although hyperammonemia may be asymptomatic, clinical symptoms of hyperammonemic encephalopathy often include acute alterations in level of consciousness and/or cognitive function with lethargy and/or vomiting. This hyperammonemia and encephalopathy can develop with EPRONTIA treatment alone or with EPRONTIA treatment with concomitant valproic acid (VPA).

Instruct patients to contact their physician if they develop unexplained lethargy, vomiting, or changes in mental status [see Warnings and Precautions (5.12)].

Kidney Stones

Instruct patients, particularly those with predisposing factors, to maintain an adequate fluid intake in order to minimize the risk of kidney stone formation [see Warnings and Precautions (5.13)].

Administration Instructions

Counsel patients that EPRONTIA may be taken with or without food. Advise patients that the dosage of EPRONTIA should be measured using a calibrated measuring device and not a household teaspoon and they may ask their pharmacist for an oral dosing syringe if you do not have one. Instruct patients to discard any unused EPRONTIA after 90 days of first opening the bottle [see Dosage and Administration (2.4)] .

Instructions for a Missing Dose

Instruct patients that if they miss a single dose of EPRONTIA, it should be taken as soon as possible. However, if a patient is within 6 hours of taking the next scheduled dose, tell the patient to wait until then to take the usual dose of EPRONTIA, and to skip the missed dose. Tell patients that they should not take a double dose in the event of a missed dose. Advise patients to contact their healthcare provider if they have missed a dose.

EPRONTIA is a registered trademark of Azurity Pharmaceuticals, Inc.

Manufactured for:
Azurity Pharmaceuticals, Inc.
Woburn, MA 01801

Patent: https://azurity.com/patents_and_trademarks/

This product's labeling may have been updated. For current Full Prescribing Information, please visit www.eprontia.com

PN: 65628-00603

REV #: 09

Medication Guide

EPRONTIA®

[ee-pron-tee-ah]

(topiramate) oral solution

What is the most important information I should know about EPRONTIA?

EPRONTIA may cause eye problems.Serious eye problems include:

- any sudden decrease in vision with or without eye pain and redness.
- a blockage of fluid in the eye causing increased pressure in the eye (secondary angle closure glaucoma).
- These eye problems can lead to permanent loss of vision if not treated.
- You should call your healthcare provider right away if you have any new eye symptoms, including any new problems with your vision.

EPRONTIA may cause decreased sweating and increased body temperature (fever).People, especially children, should be watched for signs of decreased sweating and fever, especially in hot temperatures. Some people may need to be hospitalized for this condition. If a high fever, a fever that does not go away, or decreased sweating develops, call your healthcare provider right away.

EPRONTIA can increase the level of acid in your blood (metabolic acidosis). If left untreated, metabolic acidosis can cause brittle or soft bones (osteoporosis, osteomalacia, osteopenia), kidney stones, can slow the rate of growth in children, and may possibly harm your baby if you are pregnant. Metabolic acidosis can happen with or without symptoms. Sometimes people with metabolic acidosis will:

- feel tired
- not feel hungry (loss of appetite)
- feel changes in heartbeat
- have trouble thinking clearly

Your healthcare provider should do a blood test to measure the level of acid in your blood before and during your treatment with EPRONTIA. If you are pregnant, you should talk to your healthcare provider about whether you have metabolic acidosis.

Like other antiepileptic drugs, EPRONTIA may cause suicidal thoughts or actions in a very small number of people, about 1 in 500.

Call a healthcare provider right away if you have any of these symptoms, especially if they are new, worse, or worry you:

- thoughts about suicide or dying
- new or worse depression
- feeling agitated or restless
- trouble sleeping (insomnia)
- acting aggressive, being angry, or violent
- an extreme increase in activity and talking (mania)

- attempts to commit suicide
- new or worse anxiety
- panic attacks
- new or worse irritability
- acting on dangerous impulses
- other unusual changes in behavior or mood

Do not stop EPRONTIA without first talking to a healthcare provider.

- Stopping EPRONTIA suddenly can cause serious problems.
- Suicidal thoughts or actions can be caused by things other than medicines. If you have suicidal thoughts or actions, your healthcare provider may check for other causes.

How can I watch for early symptoms of suicidal thoughts and actions?

- Pay attention to any changes, especially sudden changes, in mood, behaviors, thoughts, or feelings.
- Keep all follow-up visits with your healthcare provider as scheduled.
- Call your healthcare provider between visits as needed, especially if you are worried about symptoms.

EPRONTIA can harm your unborn baby.

- If you take EPRONTIA during pregnancy, your baby has a higher risk for birth defects including cleft lip and cleft palate. These defects can begin early in pregnancy, even before you know you are pregnant.
- Birth defects may happen even in children born to women who are not taking any medicines and do not have other risk factors.
- There may be other medicines to treat your condition that have a lower chance of birth defects.
- All women of childbearing age should talk to their healthcare providers about using other possible treatments instead of EPRONTIA. If the decision is made to use EPRONTIA, you should use effective birth control (contraception) unless you are planning to become pregnant. You should talk to your doctor about the best kind of birth control to use while you are taking EPRONTIA.
- Tell your healthcare provider right away if you become pregnant while taking EPRONTIA. You and your healthcare provider should decide if you will continue to take EPRONTIA while you are pregnant.
- If you take EPRONTIA during pregnancy, your baby may be smaller than expected at birth. The long-term effects of this are not known. Talk to your healthcare provider if you have questions about this risk during pregnancy.
- Metabolic acidosis may have harmful effects on your baby. Talk to your healthcare provider if EPRONTIA has caused metabolic acidosis during your pregnancy.
- Pregnancy Registry: If you become pregnant while taking EPRONTIA, talk to your healthcare provider about registering with the North American Antiepileptic Drug Pregnancy Registry. You can enroll in this registry by calling 1-888-233-2334. The purpose of this registry is to collect information about the safety of EPRONTIA and other antiepileptic drugs during pregnancy.

EPRONTIA may decrease the density of bones when used over a long period.

EPRONTIA may slow height increase and weight gain in children and adolescents when used over a long period.

What is EPRONTIA?

EPRONTIA is a prescription medicine used:

• to treat certain types of seizures (partial-onset seizures and primary generalized tonic-clonic seizures) in adults and children 2 years and older.

• with other medicines to treat certain types of seizures (partial-onset seizures, primary generalized tonic-clonic seizures, and seizures associated with Lennox-Gastaut syndrome) in adults and children 2 years and older.

• to prevent migraine headaches in adults and adolescents 12 years and older.

Before taking EPRONTIA, tell your healthcare provider about all of your medical conditions, including if you:

- have or have had depression, mood problems, or suicidal thoughts or behavior.
- have kidney problems, have kidney stones, or are getting kidney dialysis.
- have a history of metabolic acidosis (too much acid in the blood).
- have liver problems.
- have weak, brittle, or soft bones (osteomalacia, osteoporosis, osteopenia, or decreased bone density).
- have lung or breathing problems.
- have eye problems, especially glaucoma.
- have diarrhea.
- have a growth problem.
- are on a diet high in fat and low in carbohydrates, which is called a ketogenic diet.
- are having surgery.
- are pregnant or plan to become pregnant.
- are breastfeeding or plan to breastfeed. EPRONTIA passes into breast milk. Breastfed babies may be sleepy or have diarrhea. It is not known if the EPRONTIA that passes into breast milk can cause other serious harm to your baby. Talk to your healthcare provider about the best way to feed your baby if you take EPRONTIA.

Tell your healthcare provider about all the medicines you take, including prescription and over-the-counter medicines, vitamins, and herbal supplements. EPRONTIA and other medicines may affect each other causing side effects.

Especially tell your healthcare provider if you take:

- Valproic acid (such as DEPAKOTE).
- any medicines that impair or decrease your thinking, concentration, or muscle coordination.
- birth control that contains hormones (such as pills, implants, patches, or injections). EPRONTIA may make your birth control less effective. Tell your healthcare provider if your menstrual bleeding changes while you are using birth control and EPRONTIA.

Ask your healthcare provider if you are not sure if your medicine is listed above.

Know the medicines you take. Keep a list of them to show your healthcare provider and pharmacist each time you get a new medicine. Do not start a new medicine without talking with your healthcare provider.

How should I take EPRONTIA?

- Take EPRONTIA Oral Solution exactly as prescribed.
- Your healthcare provider may change your dose. Do not change your dose without talking to your healthcare provider.
- EPRONTIA can be taken with or without food. Drink plenty of fluids during the day. This may help prevent kidney stones while taking EPRONTIA.
- Take EPRONTIA using a marked (calibrated) measuring device. Ask your pharmacist to recommend a measuring device and for instructions on how to measure the correct dose. Do not use a household teaspoon or tablespoon.
- If you take too much EPRONTIA, call your healthcare provider right away or go to the nearest emergency room.
- If you miss a single dose of EPRONTIA, take it as soon as you can. However, if you are within 6 hours of taking your next scheduled dose, wait until then to take your usual dose of EPRONTIA, and skip the missed dose. Do not double your dose. If you have missed more than 1 dose, you should call your healthcare provider for advice.
- Do not stop taking EPRONTIA without talking to your healthcare provider. Stopping EPRONTIA suddenly may cause serious problems. If you have epilepsy and you stop taking EPRONTIA suddenly, you may have seizures that do not stop. Your healthcare provider will tell you how to stop taking EPRONTIA slowly. Your healthcare provider may do blood tests while you take EPRONTIA.

What should I avoid while taking EPRONTIA?

- You should not drink alcohol while taking EPRONTIA. EPRONTIA and alcohol can affect each other causing side effects such as sleepiness and dizziness.
- Do not drive a car or operate machinery until you know how EPRONTIA affects you. EPRONTIA can slow your thinking and motor skills and may affect vision.

What are the possible side effects of EPRONTIA? EPRONTIA may cause serious side effects including:

See " What is the most important information I should know about EPRONTIA?"

- High blood ammonia levels. High ammonia in the blood can affect your mental activities, slow your alertness, make you feel tired, or cause vomiting. This has happened when EPRONTIA is taken with a medicine called valproic acid (DEPAKOTE). Call your healthcare provider right away if you develop unexplained tiredness, vomiting, slowing of your thinking or reaction time, or changes in your mental activities.
- Effects on thinking and alertness. EPRONTIA may affect how you think and cause confusion, problems with concentration, attention, memory, or speech. EPRONTIA may cause depression or mood problems, tiredness, and sleepiness.
- Dizziness or loss of muscle coordination.
- Serious skin reactions. EPRONTIA may cause a severe rash with blisters and peeling skin, especially around the mouth, nose, eyes, and genitals (Stevens-Johnson syndrome). EPRONTIA may also cause a rash with blisters and peeling skin over much of the body that may cause death (toxic epidermal necrolysis). Call your healthcare provider right away if you develop a skin rash or blisters.
- Kidney stones. Drink plenty of fluids when taking EPRONTIA to decrease your chances of getting kidney stones.
- Low body temperature. Taking EPRONTIA when you are also taking valproic acid can cause a drop in body temperature to less than 95°F, or can cause tiredness, confusion, or coma.

Call your healthcare provider right away if you have any of the symptoms above.

The most common side effects of EPRONTIA include:

o tingling of the arms and legs (paresthesia)
o nausea
o diarrhea
o nervousness
o speech problems
o dizziness
o slow reactions
o pain in the abdomen
o decreased feeling or sensitivity, especially in the skin

o not feeling hungry

o a change in the way foods taste

o weight loss

o upper respiratory tract infection

o tiredness

o sleepiness/drowsiness

o difficulty with memory

o fever

o abnormal vision

Tell your healthcare provider about any side effect that bothers you or that does not go away. These are not all the possible side effects of EPRONTIA. Call your doctor for medical advice about side effects. You may report side effects to FDA at 1- 800-FDA-1088. You may also report side effects to Azurity Pharmaceuticals, Inc. at 1-800-461-7449.

How should I store EPRONTIA?

- Store EPRONTIA at room temperature between 68°F to 77°F (20°C to 25°C).
- Throw away (discard) unused portion 90 days after first opening.
- Avoid freezing and excessive heat.
- Keep container tightly closed

Keep EPRONTIA and all medicines out of the reach of children.

General information about the safe and effective use of EPRONTIA.

Medicines are sometimes prescribed for purposes other than those listed in a Medication Guide. Do not use EPRONTIA for a condition for which it was not prescribed. Do not give EPRONTIA to other people, even if they have the same symptoms that you have. It may harm them. You can ask your pharmacist or healthcare provider for information about EPRONTIA that is written for health professionals.

What are the ingredients in EPRONTIA?

Active ingredient:Topiramate

Inactive ingredients: glycerin, methylparaben, mixed berry flavor, polyethylene glycol, propylparaben, and sucralose.

Manufactured for:
Azurity Pharmaceuticals, Inc.
Woburn, MA 01801

This Medication Guide has been approved by the U.S. Food and Drug Administration

Approved: May 2024

PRINCIPAL DISPLAY PANEL - Carton Label

Carton Label

NDC 52652-9001-2

EPRONTIA®(topiramate)
oral solution

25 mg/mL

FOR ORAL USE ONLY

ATTENTION PHARMACIST:

Dispense the following to each patient:

•Oral Dosing Syringe

•Medication Guide - available at
eprontia.com/medication-guide.pdf

READY TO USE

240 mL Rx Only

azurity®pharmaceuticals

Manufactured for:
Azurity Pharmaceuticals, Inc.
Woburn, MA 01801